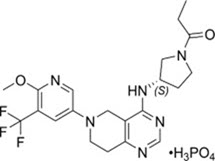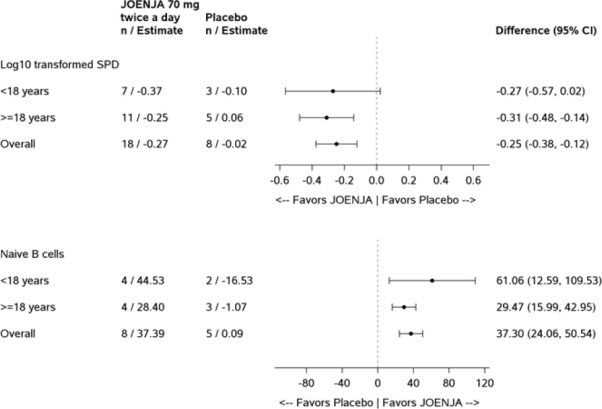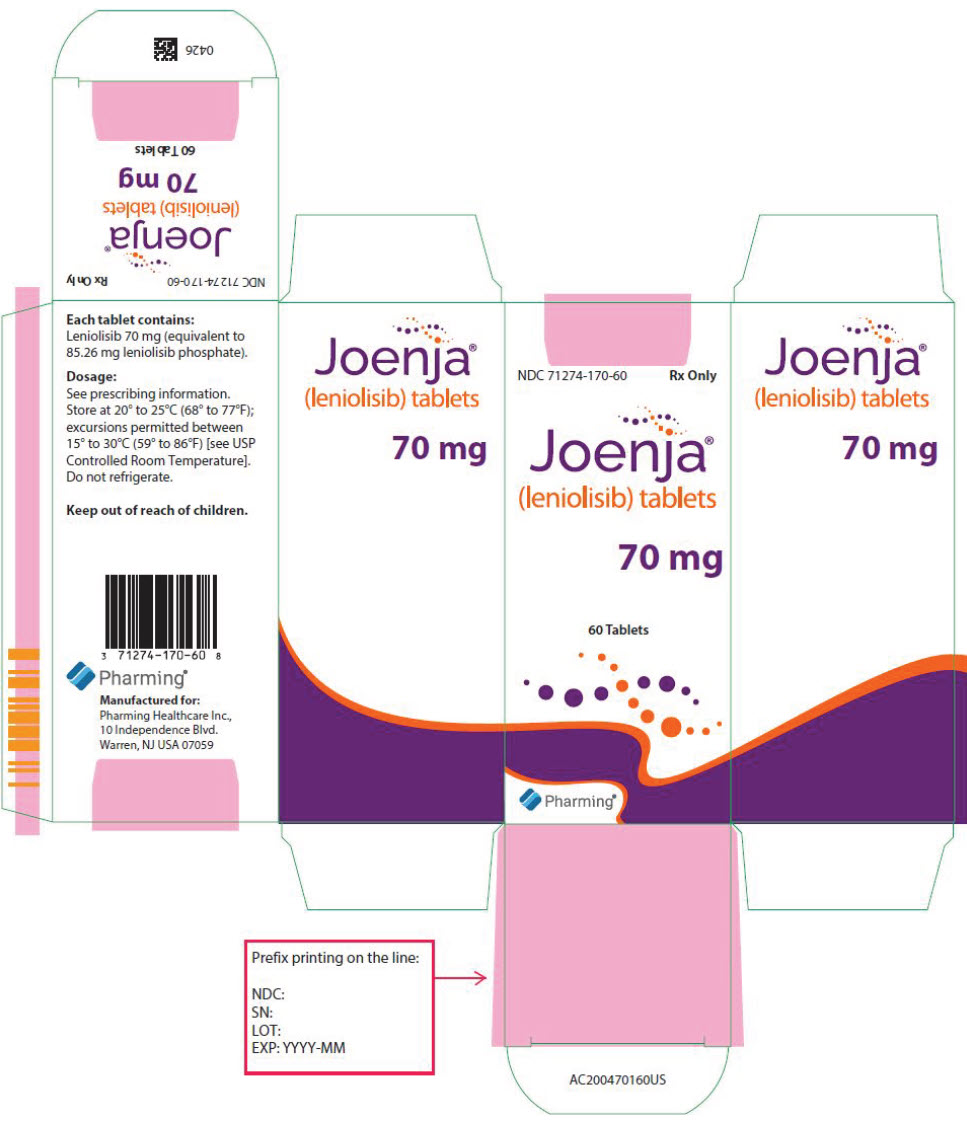 DRUG LABEL: Joenja
NDC: 71274-170 | Form: TABLET, FILM COATED
Manufacturer: Pharming Healthcare Inc.
Category: prescription | Type: HUMAN PRESCRIPTION DRUG LABEL
Date: 20250605

ACTIVE INGREDIENTS: Leniolisib phosphate 70 mg/1 1

HIGHLIGHTS OF PRESCRIBING INFORMATION

These highlights do not include all the information needed to use JOENJA safely and effectively. See full prescribing information for JOENJA.
JOENJA® (leniolisib) tablets, for oral use
Initial U.S. Approval: 2023

RECENT MAJOR CHANGES

Warnings and Precautions, Hypersensitivity Reactions, Including Anaphylaxis (5.3) | 05/2025

1 INDICATIONS AND USAGE

JOENJA is a kinase inhibitor indicated for the treatment of activated phosphoinositide 3-kinase delta (PI3Kδ) syndrome (APDS) in adult and pediatric patients 12 years of age and older. (1)

2 DOSAGE AND ADMINISTRATION

- Verify pregnancy status in females of reproductive potential prior to initiating treatment. (2.1, 5.1)
- Recommended dosage: 70 mg administered orally twice daily approximately 12 hours apart, with or without food, in adult and pediatric patients 12 years of age and older and weighing ≥ 45kg. (2.2)

3 DOSAGE FORMS AND STRENGTHS

Tablets: 70 mg leniolisib (3)

4 CONTRAINDICATIONS

None. (4)

5 WARNINGS AND PRECAUTIONS

- Embryo-Fetal Toxicity: JOENJA may cause fetal harm. Advise patients of the potential risk to a fetus and to use effective contraception. (5.1, 8.1, 8.3)
- Vaccinations: Live, attenuated vaccinations may be less effective if administered during JOENJA treatment. (5.2)
- Risk of Hypersensitivty Reactions Including Anaphylaxis: Hypersensitivity reactions including anaphlyaxis have been reported in the postmarketing setting. If hypersensitivity reactions occur, discontinue JOENJA and institute appropriate therapy. (5.3)

6 ADVERSE REACTIONS

Most common adverse reactions (incidence > 10%) were headache, sinusitis, and atopic dermatitis. (6.1)

To report SUSPECTED ADVERSE REACTIONS, contact Pharming Healthcare Inc. at 1-800-930-5221 or FDA at 1-800-FDA-1088 or www.fda.gov/medwatch.

7 DRUG INTERACTIONS

- Strong CYP3A4 Inhibitors: Avoid concomitant use. (7.1)
- Strong and Moderate CYP3A4 Inducers: Avoid concomitant use. (7.1)
- BCRP, OATP1B1, and OATP1B3 Substrates: Avoid concomitant use. (7.2)

8 USE IN SPECIFIC POPULATIONS

- Lactation: Advise women not to breastfeed. (8.2)
- Hepatic impairment: Use in patients with moderate to severe hepatic impairment is not recommended. (8.6)

FULL PRESCRIBING INFORMATION

1 INDICATIONS AND USAGE

JOENJA is indicated for the treatment of activated phosphoinositide 3-kinase delta (PI3Kδ) syndrome (APDS) in adult and pediatric patients 12 years of age and older.

2 DOSAGE AND ADMINISTRATION

2.1 Testing Prior to Treatment with JOENJA

Verify pregnancy status in females of reproductive potential prior to initiating treatment with JOENJA [see Warnings and Precautions (5.1), and Use in Specific Populations (8.1, 8.3)].

2.2 Recommended Dosage and Administration

The recommended dosage of JOENJA in adult and pediatric patients 12 years of age and older weighing 45 kg or greater is 70 mg administered orally twice daily approximately 12 hours apart, with or without food. There is no recommended dosage for patients weighing less than 45 kg.

Advise patients that if a dose is missed by more than 6 hours, wait and take the next dose at the usual time.

Advise patients that if vomiting occurs within 1 hour after taking JOENJA, take JOENJA as soon as possible. If vomiting occurs more than 1 hour after dosing, wait and take the next dose at the usual time.

3 DOSAGE FORMS AND STRENGTHS

Tablets: 70 mg (leniolisib), yellow, oval-shaped, biconvex, bevelled edge film-coated tablet debossed with "70" on one side and "LNB" on the other side.

4 CONTRAINDICATIONS

None.

5 WARNINGS AND PRECAUTIONS

5.1 Embryo-Fetal Toxicity

Based on findings in animals, JOENJA may cause fetal harm when administered to a pregnant woman. Administration of leniolisib to rats and rabbits during the period of organogenesis caused embryo-fetal toxicity including malformations at exposures that were 2-6 times higher than the maximum recommended human dose (MRHD) in APDS patients based on AUC comparisons. Verify the pregnancy status of patients of reproductive potential prior to starting treatment. Advise pregnant women of the potential risk to a fetus. Advise females of reproductive potential to use highly effective methods of contraception during treatment and for 1 week after the last dose [see Dosage and Administration (2.1), Use in Specific Populations (8.1, 8.3)].

5.2 Vaccinations

Live, attenuated vaccinations may be less effective if administered during JOENJA treatment.

5.3 Risk of Hypersensitivity Reactions, Including Anaphylaxis

Hypersensitivity reaction(s), including anaphylaxis, have been reported in postmarketing setting. If a clinically significant hypersensitivity reaction occurs, discontinue JOENJA and institute appropriate therapy [see Adverse Reactions (6.2)].

6 ADVERSE REACTIONS

The following clinically significant adverse reactions are described elsewhere in the labeling:

- Risk of Hypersensitivity Reactions, Including Anaphylaxis [see Warnings and Precautions (5.3)]

6.1 Clinical Trials Experience

Because clinical trials are conducted under widely varying conditions, adverse reaction rates observed in the clinical trials of a drug cannot be directly compared to rates in the clinical trials of another drug and may not reflect the rates observed in practice.

The safety of JOENJA reflects exposure based on 38 adult and pediatric patients 12 years of age and older with activated phosphoinositide 3-kinase delta (PI3Kδ) syndrome (APDS) from the placebo-controlled portion of Study 2201 [see Clinical Studies (14)] and additional open-label clinical safety data. Thirty-seven of 38 patients received JOENJA 70 mg orally twice daily for at least 25 weeks and 66% were exposed for 96 weeks or longer. Median duration of JOENJA treatment was approximately 2 years, and 4 patients had more than 5 years of JOENJA exposure.

The data below are based on the 12-week, placebo-controlled portion of Study 2201 in which either JOENJA 70 mg (N=21) or placebo (N=10) was administered twice daily to patients with APDS. Demographics of the patients who participated in this study are summarized in Clinical Studies [see Clinical Studies (14)]. Table 1 presents the number of patients and incidence, rounded to the nearest percent, of adverse reactions that occurred in 2 or more patients treated with JOENJA and for which the incidence in patients treated with JOENJA was greater than the incidence in patients treated with placebo.

The most common adverse reactions (> 10%) were headache, sinusitis, and atopic dermatitis.

Table 1 Adverse Reactions Reported by 2 or More JOENJA-Treated Patients and More Frequently than Placebo
Adverse Reactions | JOENJA N=21 n (%) | Placebo N=10 n (%)
Headache | 5 (24) | 2 (20)
Sinusitis | 4 (19) | 0
Dermatitis atopic^1 | 3 (14) | 0
Tachycardia^2 | 2 (10) | 0
Diarrhea | 2 (10) | 0
Fatigue | 2 (10) | 1 (10)
Pyrexia | 2 (10) | 0
Back pain | 2 (10) | 0
Neck pain | 2 (10) | 0
Alopecia | 2 (10) | 0
^1Dermatitis atopic: including dermatitis atopic and eczema
^2Tachycardia: including tachycardia and sinus tachycardia

Specific Adverse Reactions

Laboratory Abnormalities

Seven (33%) patients receiving JOENJA developed an absolute neutrophil count (ANC) between 500 and 1500 cells/microL. No patients developed an ANC < 500 cells/microL and there were no reports of infection associated with neutropenia.

Weight Increase

In the open-label clinical trial (n=37), five patients (14%) experienced weight gain. Some patients became overweight or obese.

6.2 Postmarketing Experience

The following adverse reactions have been identified during postapproval use of JOENJA. Because these reactions are reported voluntarily from a population of uncertain size, it is not always possible to reliably estimate their frequency or establish a causal relationship to drug exposure.

Immune System Disorders: hypersensitivity (anaphylaxis)

7 DRUG INTERACTIONS

7.1 Effects of Other Drugs on JOENJA

Strong CYP3A4 Inhibitors

Concomitant use of JOENJA with strong CYP3A4 inhibitors should be avoided.

JOENJA is a substrate of CYP3A4. Leniolisib exposure was increased 2-fold when co-administered with itraconazole, a strong CYP3A4 inhibitor [see Clinical Pharmacology (12.3)].

Strong and Moderate CYP3A4 Inducers

Concomitant use of JOENJA with strong and moderate CYP3A4 inducers should be avoided.

JOENJA is a substrate of CYP3A4. Concomitant use of strong and moderate CYP3A4 inducers may result in reduced leniolisib exposure and thus reduced leniolisib efficacy [see Clinical Pharmacology (12.3)].

7.2 Effects of JOENJA on Other Drugs

BCRP, OATP1B1, and OATP1B3 Substrates

Concomitant use of JOENJA with BCRP, OATP1B1, and OATP1B3 substrates should be avoided.

JOENJA is an inhibitor of BCRP, OATP1B1, and OATP1B3 transporters. Administration of JOENJA increases exposure of BCRP, OATP1B1, and OATP1B3 substrates [see Clinical Pharmacology (12.3)], which may increase the risk of adverse reactions related to these substrates.

8 USE IN SPECIFIC POPULATIONS

8.1 Pregnancy

Risk Summary

JOENJA can cause fetal harm based on findings from animal studies. There are no available data on JOENJA use in pregnant women to inform a drug-associated risk of major birth defects, miscarriage, or other adverse maternal or fetal outcomes.

In animal reproduction studies, oral administration of leniolisib to pregnant rats and rabbits during the period of organogenesis at exposures approximately 2-6 times the MRHD on an AUC basis, produced embryofetal toxicity including malformations (see Data). Advise pregnant women of the potential risk to a fetus.

The background risk of major birth defects and miscarriage for the indicated population is unknown. All pregnancies have a background risk of birth defect, loss, or other adverse outcomes. In the U.S. general population, the estimated background risk of major birth defects and miscarriage of clinically recognized pregnancies is 2% to 4% and 15% to 20%, respectively.

Data

Animal Data

Leniolisib was administered orally to pregnant rats at doses of 10, 30, and 120 mg/kg/day during the period of organogenesis from gestation Day 6 to Day 17. Leniolisib at a dose of 120 mg/kg/day was associated with decreased fetal body weight, visceral and skeletal variations, and external, visceral, and skeletal malformations (eye bulge, microphthalmia, anophthalmia, and reduction in orbital socket size) in the presence of maternal toxicity (decrease in body weight gain) at exposures approximately 6 times the MRHD on an AUC basis. No developmental toxicity was observed in rats at an exposure approximately 2 times the MRHD (on an AUC basis at a maternal oral dose of 30 mg/kg/day).

Leniolisib was administered orally to pregnant rabbits at doses of 10, 30, and 100 mg/kg/day during the period of organogenesis from gestation Day 7 to Day 20. Leniolisib at a dose of 100 mg/kg/day was associated with skeletal variations as well as visceral and skeletal malformations (microphthalmia and reduction in orbital socket size) in the presence of maternal toxicity (decrease in body weight gain) at exposures approximately 2 times the MRHD on an AUC basis. No developmental toxicity was observed in rabbits at an exposure approximately 0.3 times the MRHD (on an AUC basis at a maternal oral dose of 30 mg/kg/day).

In a pre- and postnatal developmental toxicity study, leniolisib was administered orally to pregnant rats at oral doses of 10, 30, and 90 mg/kg/day from gestation day 7 through postnatal day 21. Leniolisib at a dose of 90 mg/kg/day (approximately 5 times the exposure at the MRHD on an AUC basis) was associated with a slight decrease in the percentage of pups born that survived 21 days postpartum (lactation index) and decreased pup body weights were observed prior to weaning.

8.2 Lactation

Risk Summary

There are no data on the presence of leniolisib or its metabolites in human milk or the effects on the breastfed infant or milk production. Leniolisib is present in rat milk (see Data). When a drug is present in animal milk, it is likely that the drug will be present in human milk. Because of the potential for serious adverse reactions from leniolisib in the breastfed child, advise women not to breastfeed during treatment with JOENJA and for 1 week after the last dose.

Data

Animal Data

Leniolisib was present in the milk of lactating rats administered oral doses of 10, 30, and 90 mg/kg/day from gestation day 7 through postnatal day 21. Leniolisib concentrations were approximately 2- to 3-fold higher in milk than in maternal plasma. The concentration of leniolisib in animal milk does not necessarily predict the concentration of drug in human milk.

8.3 Females and Males of Reproductive Potential

Based on findings from animal studies, JOENJA may cause fetal harm when administered to a pregnant woman [see Use in Specific Populations (8.1)].

Pregnancy Testing

Verify the pregnancy status in females of reproductive potential prior to initiating JOENJA.

Contraception

Females

Advise female patients of reproductive potential to use highly effective contraception during treatment with JOENJA and to continue contraception for 1 week after the last dose.

8.4 Pediatric Use

The safety and effectiveness of JOENJA for the treatment of activated phosphoinositide 3-kinase delta syndrome have been established in pediatric patients 12 years of age and older. Use of JOENJA for this indication is supported by evidence from an adequate and well-controlled study in adult and pediatric patients 12 years of age and older [see Clinical Studies (14)]. There is no recommended dosage for pediatric patients 12 years of age and older who weigh less than 45 kg [see Dosage and Administration (2.2)].

The safety and effectiveness of JOENJA have not been established in pediatric patients below the age of 12 years.

Juvenile Animal Toxicity Data

Studies were conducted with leniolisib in juvenile rats starting at postnatal day (PND) 7 (the equivalent of a human newborn) to PND 77 (the equivalent of a human adult). Death was observed in juvenile rats that received 90 mg/kg/day, approximately 2-4 times the MRHD on an AUC basis and occurred primarily during the pre-weaning period (PND 9 to PND 15). Changes in the onset of puberty (delays in males and accelerations in females) were observed in juvenile rats at equal to or greater than 30 mg/kg/day leniolisib, which is one half to equivalent to, the MRHD on an AUC basis. A no effect dose level was identified at an exposure approximately 0.2 times the MRHD on an AUC basis.

8.5 Geriatric Use

Because clinical studies of JOENJA did not include any patients 65 years of age and older, it cannot be determined whether they respond differently from younger adult patients.

8.6 Hepatic Impairment

Leniolisib is extensively (60%) metabolized by the liver. The effect of hepatic impairment on the pharmacokinetics of leniolisib has not been studied. The use of JOENJA in patients with moderate to severe hepatic impairment is not recommended [see Clinical Pharmacology (12.3)].

10 OVERDOSAGE

If overdosage occurs, monitor the patient for any signs or symptoms of adverse reactions. Treatment of overdose with JOENJA consists of general supportive measures including monitoring of vital signs as well as observation of the clinical status of the patient.

11 DESCRIPTION

Leniolisib is a kinase inhibitor. The chemical name for leniolisib phosphate is 1-[(3S)-3-[[5,6,7,8-Tetrahydro-6-[6-methoxy-5-(trifluoromethyl)-3-pyridinyl]pyrido[4,3-d]pyrimidin-4-yl]amino]-1-pyrrolidinyl]-1-propanone phosphate (1:1).

Leniolisib phosphate has the following structural formula:

The molecular formula is C21H25F3N6O2•H3PO4 and the molecular weight is 450.47 g/mol for the free base, 548.46 g/mol for the phosphate salt.

Leniolisib phosphate is a white to yellowish to yellowish-greenish powder. The aqueous solubility of leniolisib phosphate is pH dependent with decreasing solubility observed with increasing pH.

JOENJA film-coated tablets are for oral administration. Each tablet contains 70 mg of leniolisib (equivalent to 85.26 mg leniolisib phosphate) with the following inactive ingredients: colloidal silicon dioxide, hydroxypropyl methylcellulose, lactose monohydrate, magnesium stearate, microcrystalline cellulose, and sodium starch glycolate. The tablet filmcoating contains hydroxypropyl methylcellulose, iron oxide red, iron oxide yellow, polyethylene glycol, talc, and titanium dioxide.

12 CLINICAL PHARMACOLOGY

12.1 Mechanism of Action

Leniolisib inhibits PI3K-delta by blocking the active binding site of PI3K-delta. In cell-free isolated enzyme assays, leniolisib was selective for PI3K-delta over PI3K-alpha (28-fold), PI3K-beta (43-fold), and PI3K-gamma (257-fold), as well as the broader kinome. In cell-based assays, leniolisib reduced pAkt pathway activity and inhibited proliferation and activation of B and T cell subsets. Gain-of-function variants in the gene encoding the p110-delta catalytic subunit or loss of function variants in the gene encoding the p85-alpha regulatory subunit each cause hyperactivity of PI3K-delta. Leniolisib inhibits the signalling pathways that lead to increased production of PIP3, hyperactivity of the downstream mTOR/Akt pathway, and to the dysregulation of B and T cells.

12.2 Pharmacodynamics

Ex vivo pharmacodynamics of leniolisib [proportion of phosphorylated Akt (pAkt)-positive B cells] were assessed intra-individually at 10, 30, and 70 mg twice daily for 4 weeks at each dose level in patients with APDS. Within the explored dose range, higher leniolisib plasma concentrations were generally associated with higher reduction of pAkt-positive B cells and higher doses were associated with a slightly higher peak reduction as well as more sustained reduction. Treatment with JOENJA 70 mg twice a day at steady state is estimated to produce time-averaged reduction of pAkt-positive B cells by approximately 80%.

12.3 Pharmacokinetics

The systemic drug exposure (AUC and Cmax) of leniolisib increased dose proportionally within the studied range of doses (20 to 140 mg twice a day dosing and single doses of 10 to 400 mg). During twice daily dosing approximately 12 hours apart, leniolisib accumulates approximately 1.4-fold (range of 1.0 to 2.2) in achieving steady-state, consistent with an effective half-life (t1/2) of approximately 7 hours. Steady state drug concentrations can be expected to be reached after approximately 2 to 3 days of JOENJA treatment. The pharmacokinetics of leniolisib are similar between healthy participants and APDS patients.

Absorption

In a placebo controlled, single and multiple ascending dose study in healthy participants, leniolisib median time to maximum plasma concentration (Tmax) occurred at about 1 hour postdose. Tmax appeared independent of dose and was not altered after multiple oral doses. Food is unlikely to have a clinically meaningful effect on the systemic exposure of leniolisib during JOENJA treatment.

Distribution

The systemic decay in leniolisib plasma concentration over time is bi-exponential, indicating a distribution delay towards peripheral tissues. The apparent terminal elimination t1/2 is approximately 10 hours. The volume of distribution of leniolisib is estimated to be 28.5 L in patients with APDS. Leniolisib was highly bound (94.5%) to plasma proteins.

Elimination

The mean recovery of total 14C-radioactivity following a single oral dose of 70 mg 14C-leniolisib was 92.5% (67.0% and 25.5% recovered via feces and urine, respectively) 168 hours postdose. Unchanged leniolisib (6.32%) was the predominant drug-related material recovered in urine.

Metabolism

Leniolisib was 60% metabolized by the liver, with CYP3A4 being the most predominant enzyme involved (95.4%) in the primary oxidative metabolism of leniolisib with minor contribution from other enzymes (3.5% CYP3A5, 0.7% CYP1A2 and 0.4% CYP2D6). Intestinal secretion by BCRP as well as extrahepatic CYP1A1 cannot be excluded as excretion routes.

Specific Populations

Pediatric Patients

Following a single 70 mg oral dose of leniolisib in APDS patients, leniolisib systemic exposures were comparable between pediatric patients (12 to 17 years of age) and adults (≥ 18 years of age), with median Tmax (ranging from 1 to 5 hours) reached approximately 3 hours post-dose in patients 12 to 17 years of age. The observed difference in the median Tmax between pediatric patients (12 to 17 years of age) and adults (≥ 18 years of age) is not clinically relevant given the PK variability and comparable concentration-time profiles between the two age groups.

Patients with Hepatic Impairment

The effect of hepatic impairment on the pharmacokinetics of leniolisib has not been evaluated. As leniolisib is metabolized to a large extent by the liver (60%), use of JOENJA is not recommended in patients with moderate to severe hepatic impairment [see Specific Populations (8.6)].

Drug Interaction Studies

Strong CYP3A4 Inhibitors: Leniolisib-exposure was increased approximately 2-fold when administered with itraconazole (strong CYP3A4 inhibitor).

Moderate CYP3A4 Inhibitors: Physiological based pharmacokinetic (PBPK) model-based simulations predicted a maximum increase of 75% in leniolisib AUC0-12 with erythromycin (moderate CYP3A4 inhibitor).

CYP3A4 Inducers: PBPK model-based simulations predicted a maximum decrease of 78% and 58% in leniolisib AUC0-12 with rifampin (strong CYP3A4 inducer) and efavirenz (moderate CYP3A4 inducer), respectively.

CYP2D6 and P-gp inhibitors: Quinidine (strong P-gp and CYP2D6 inhibitor) had no effect on leniolisib systemic exposure. Leniolisib is not a sensitive substrate of P-gp and CYP2D6.

Oral Contraceptives: When combined with a monophasic oral contraceptive containing levonorgestrel and ethinylestradiol, leniolisib increased ethinylestradiol exposure by approximately 25 to 30% in terms of both AUC and Cmax, but did not affect the Cmax or AUC of levonorgestrel. Efficacy of a combined oral contraceptive composed of ethinylestradiol and levonorgestrel is not expected to be compromised by concomitant use with leniolisib.

Gastric Acid Reducing Agents: Leniolisib exhibits pH-dependent solubility (pH range of 1.2 to 4), with low solubility at higher pH values (≥ 5). However, PK results from APDS patients did not indicate that acid reducing agents (e.g., H2-antagonists, proton pump inhibitors) have a clinically relevant effect on leniolisib systemic exposure.

BCRP, OATP1B1, and OATP1B3 substrates: When co-administered, leniolisib increased rosuvastatin (a substrate of BCRP, OATP1B1, and OATP1B3) systemic exposure by 2-fold.

Other Drugs: No clinically relevant differences in the systemic exposure of caffeine (CYP1A2 substrate), furosemide (a substrate of OAT1 and OAT3), and metformin (a substrate of MATE1, MATE2-K, and OCT2) were observed following concomitant use with leniolisib.

13 NONCLINICAL TOXICOLOGY

13.1 Carcinogenesis, Mutagenesis, Impairment of Fertility

Leniolisib was not carcinogenic in the 6-month carcinogenicity study in Tg.rasH2 transgenic mice at doses up to 80 mg/kg/day.

Leniolisib was not genotoxic in the in vitro Ames assay, in vitro chromosomal aberration assay in human lymphocytes, or micronucleus assays in TK6 cells (in vitro) and rats (in vivo).

In a fertility study, male rats had decreased round spermatids and decreased spermatocytes in the testis at an oral dose of 90 mg/kg/day (approximately 2 times the MRHD on an AUC basis). Leniolisib had no effect on fertility in female rats at oral doses up to 90 mg/kg/day (approximately 4 times the MRHD on an AUC basis). No effects on male or female fertility and reproductive performance indices were observed up to the maximum dose administered of 90 mg/kg/day (approximately 2-4 times the MRHD on an AUC basis).

14 CLINICAL STUDIES

The efficacy of JOENJA was evaluated in the placebo-controlled portion of Study 2201 (NCT02435173), a 12-week blinded, randomized, placebo-controlled study in adult and pediatric patients 12 years of age and older with confirmed APDS-associated genetic PI3Kδ mutation with a documented variant in either PIK3CD or PIK3R1. Baseline patient demographics are shown in Table 2.

Table 2 Baseline Demographic and Disease Characteristics in Patients with APDS (Study 2201)
Demographics and Disease Characteristics | JOENJA (N=21) | Placebo (N=10)
Demographics
Age^1 (Years) Mean (SD) | 22.2 (10.00) | 26.7 (13.43)
Age Categories < 18, n (%) (Min, Max) ≥ 18, n (%) (Min, Max) | 8 (38) (12, 17) 13 (62) (18, 54) | 4 (40) (15, 17) 6 (60) (18, 48)
Sex, n (%) Male Female | 11 (52) 10 (48) | 4 (40) 6 (60)
Race, n (%) Asian Black White Other | 1 (5) 1 (5) 18 (86) 1 (5) | 1 (10) 1 (10) 7 (70) 1 (10)
Ethnicity, n (%) Hispanic or Latino Not Hispanic or Latino Not reported | 0 14 (67) 7 (33) | 1 (10) 7 (70) 2 (20)
Disease Characteristics
APDS 1 (PIK3CD variant), n (%) | 16 (76) | 9 (90)
APDS 2 (PIK3R1 variant), n (%) | 5 (24) | 1 (10)
Concomitant glucocorticoids, n (%) | 12 (57) | 6 (60)
Concomitant immunoglobulin G (IgG), n (%) | 14 (67) | 7 (70)
Previous rapamycin/sirolimus use, n (%) | 4 (19) | 3 (30)
^1Patient age from study Day -4 up to initial JOENJA dosing

Patients had nodal and/or extranodal lymphoproliferation, as measured by index nodal lesion selected by the Cheson methodology on CT or MRI and clinical findings and manifestations compatible with APDS (e.g., history of repeated oto-sino-pulmonary infections, organ dysfunction). Immunosuppressive medications or PI3Kδ inhibitors (selective or non-selective) were prohibited within 6 weeks of baseline (Day -1 and the visit prior to first study drug administration) and throughout the study. In addition, patients who had previous or concurrent B cell depleters (e.g., rituximab) within 6 months of baseline were excluded from the study, unless absolute B lymphocytes in the blood were normal. B cell depleters were prohibited throughout the study.

Thirty-one patients were randomized 2:1 to receive either JOENJA 70 mg (N=21) or placebo (N=10) twice a day for 12 weeks. The co-primary efficacy endpoints were improvement in lymphoproliferation as measured by a change from baseline in lymphadenopathy measured by the log10-transformed sum of product diameters and the normalization of immunophenotype as measured by the percentage of naïve B cells out of total B cells. Both co-primary efficacy endpoints were statistically significant (Table 3).

Table 3 Co-primary Endpoints in Placebo-Controlled Portion of Study 2201 at Week 12 (Day 85)
 | JOENJA (N=21) | Placebo (N=10)
Log10-Transformed SPD of Index Lesions (Excluding Patients with 0 Lesions at Baseline) a
nb | 18 | 8
Baseline Mean (SD) | 3.03 (0.42) | 3.05 (0.39)
Change from Baseline, LS Mean (SE) | -0.27 (0.04) | -0.02 (0.05)
Difference vs. Placebo (95% CI) |  | -0.25 (-0.38, -0.12)
p-value |  | 0.0006
Percentage of Naïve B Cells out of Total B Cells (Patients with < 48% of Naïve B Cells at Baseline) c
nd | 8 | 5
Baselinee Mean (SD) | 27.16 (13.16) | 30.51 (7.97)
Change from Baseline, LS Mean (SE) | 37.39 (5.34) | 0.09 (6.66)
Difference vs. Placebo (95% CI) |  | 37.30 (24.06, 50.54)
p-value |  | 0.0002
CI=confidence interval; SD= Standard deviation; SE=standard error; SPD=sum of product diameters; vs=versus; LS Mean: Least-squares mean
Note: The LS mean change from baseline, difference in LS mean change from baseline between JOENJA and placebo and its p-value were obtained from an Analysis of Covariance model with treatment, glucocorticoids use and immunoglobulin replacement therapy at baseline, and baseline measurement as covariates.
aChange in index lesion size was measured using the log10 transformed sum of the product of diameters (SPD) of the largest lymph nodes (maximum of 6) identified as per the Cheson criteria on CT/MRI.
bThe analysis excluded 2 patients from each treatment group due to protocol deviations and 1 JOENJA patient having complete resolution of the index lesion identified at baseline.
cCell surface markers used to distinguish naïve B cells on flow cytometry were CD19+ CD27- CD10-.
dThe analysis excluded 2 patients from each treatment group due to protocol deviations, 5 JOENJA patients and 3 placebo patients with more than or equal to 48% naïve B cells at baseline, 5 JOENJA patients with no Day 85 measurement, and 1 JOENJA patient with no baseline measurement.
eBaseline is defined as the arithmetic mean of the Baseline and Day 1 values when both were available, and if either value was missing, the existing value was used.

Figure 1 represents the co-primary endpoints grouped by age (< 18 years of age vs ≥ 18 years of age).

Figure 1 Difference from Baseline in Log10 Transformed SPD of Index Lesions and Percentage of Naïve B Cells out of Total B Cells (Patients with < 48% of Naïve B Cells at Baseline) by Age Group

16 HOW SUPPLIED/STORAGE AND HANDLING

JOENJA is available in 70 mg tablet: yellow, oval-shaped, biconvex, bevelled edge film-coated tablet debossed with "70" on one side and "LNB" on the other side. It is supplied in bottles with a child-resistant cap of 60 tablets (NDC 71274-170-60).

Store at 20°C to 25°C (68°F to 77°F); excursions permitted between 15°C to 30°C (59°F to 86°F) [see USP Controlled Room Temperature]. Do not refrigerate.

17 PATIENT COUNSELING INFORMATION

Embryo-Fetal Toxicity

- Advise pregnant women of the potential risk to a fetus. Advise females of reproductive potential to inform their healthcare provider of a known or suspected pregnancy. [see Warnings and Precautions (5.1) and Use in Specific Populations (8.1, 8.3)].
- Advise females of reproductive potential to use highly effective contraceptive during treatment with JOENJA and for 1 week after the last dose [see Warnings and Precautions (5.1) and Use in Specific Populations (8.3)].

Vaccinations

Instruct patients to inform the healthcare providers that they are taking JOENJA prior to a potential vaccination [see Warnings and Precautions (5.2)].

Risk of Hypersensitivity Reactions, Including Anaphylaxis

Advise patients to discontinue JOENJA and to seek immediate medical attention if they develop any signs and symptoms of serious allergic reactions [see Warnings and Precautions (5.3)].

Lactation

Advise women not to breastfeed during treatment with JOENJA and for 1 week after the last dose [see Use in Specific Populations (8.2)].

Administration

Advise patients JOENJA may be taken with or without food [see Dosage and Administration (2.2)].

Instruct patients that if they miss a dose by more than 6 hours, skip the missed dose. Advise patients to take the next dose as scheduled [see Dosage and Administration (2.2)].

Instruct patients that if vomiting occurs within 1 hour after taking JOENJA, take a dose as soon as possible [see Dosage and Administration (2.2)].

Manufactured for:
Pharming Healthcare Inc.,
10 Independence Blvd.
Warren, NJ USA 07059

JOENJA is a trademark of Pharming Intellectual Property B.V.

©2025 Pharming Technologies B.V. All rights reserved.

AC2004703US-0850

PRINCIPAL DISPLAY PANEL - 70 mg Tablet Bottle Carton

NDC 71274-170-60
Rx Only

Joenja®
(leniolisib) tablets

70 mg

60 Tablets

Pharming®